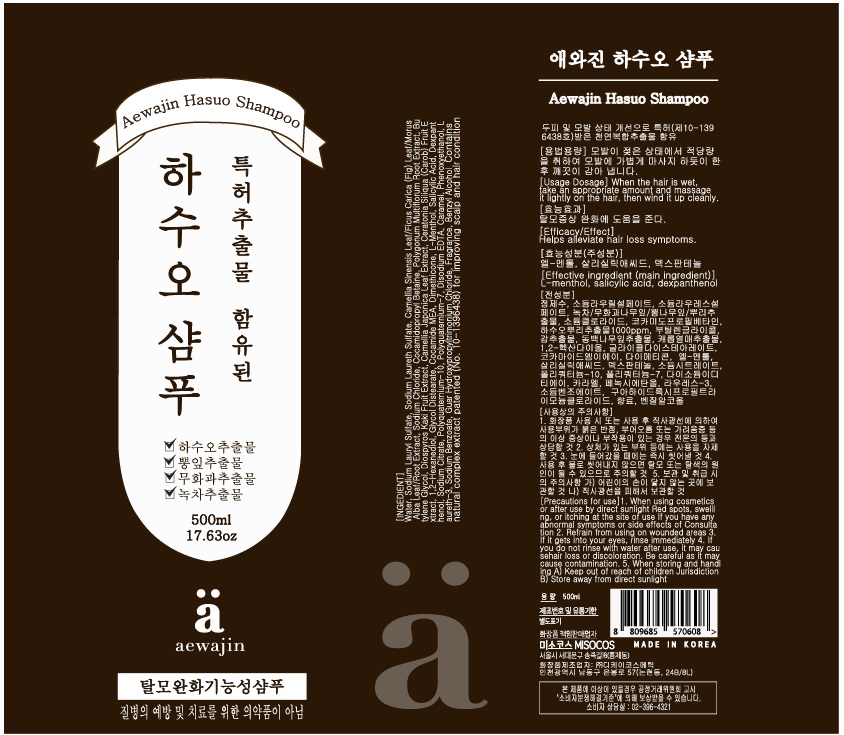 DRUG LABEL: Aewajin HasuoShampoo
NDC: 73466-0007 | Form: SHAMPOO
Manufacturer: MISOCOS
Category: otc | Type: HUMAN OTC DRUG LABEL
Date: 20220102

ACTIVE INGREDIENTS: SALICYLIC ACID 0.25 g/100 mL; MENTHOL 0.3 g/100 mL; PANTHENOL 0.2 g/100 mL
INACTIVE INGREDIENTS: WATER; GLYCERIN

ACTIVE INGREDIENT

menthol, salicylic acid, panthenol

PURPOSE

hair care, ph balanced shampoo

KEEP OUT OF REACH OF THE CHILDREN

WARNINGS

■ For external use only.

■ Do not use in eyes.

■ lf swallowed, get medical help promptly.

■ Stop use, ask doctor lf irritation occurs.

■ Keep out of reach of children.

DOSAGE AND ADMINISTRATION

for external use only

INACTIVE INGREDIENT

Water, Sodium Lauryl Sulfate, Sodium Laureth Sulfate, Camellia Sinensis Leaf/Ficus Carica (Fig) Leaf/Morus Alba
Leaf/Root Extract, Sodium Chloride, Cocamidopropyl Betaine, Polygonum Multiflorum Root Extract, Butylene
Glycol, Diospyros Kaki Fruit Extract, Camellia Japonica Leaf Extract, Ceratonia Siliqua (Carob) Fruit Extract, 1,2-
Hexanediol, Glycol Distearate, Cocamide MEA, Dimethicone, L-Menthol, Salicylic Acid, Dexpanthenol, Sodium
Citrate, Polyquaternium-10, Polyquaternium-7, Disodium EDTA, Caramel, Phenoxyethanol, Laureth-3, Sodium
Benzoate, Guar Hydroxypropyltrimonium Chloride, Fragrance, Benzyl Alcohol

INDICATIONS AND USAGE

combine hair before shampoo to remove large dust

gently massage shampoo into wet hair and scalp all over your tips

rinse to remove any remaining dubbles

tap wet hair with a toweland let it dry in natural or cold wind